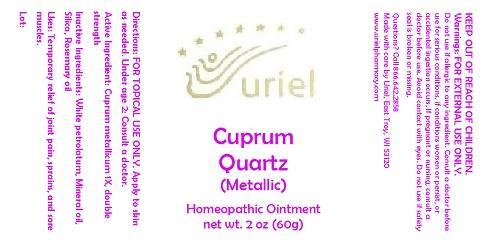 DRUG LABEL: Cuprum Quartz (Metallic)
NDC: 48951-3153 | Form: OINTMENT
Manufacturer: Uriel Pharmacy Inc.
Category: homeopathic | Type: HUMAN OTC DRUG LABEL
Date: 20140903

ACTIVE INGREDIENTS: COPPER 1 [hp_X]/1 g
INACTIVE INGREDIENTS: PETROLATUM; MINERAL OIL; COLLOIDAL SILICON DIOXIDE; ROSEMARY OIL

Cuprum Quartz (Metallic)

INDICATIONS AND USAGE

Directions: FOR TOPICAL USE ONLY.

DOSAGE AND ADMINISTRATION

Apply to skin as needed. Under age 2: Consult a doctor.

Active Ingredient: Cuprum metallicum 1X, double strength

INACTIVE INGREDIENT

Inactive Ingredients: White petrolatum, Mineral oil, Silica, Rosemary oil

PURPOSE

Uses: Temporary relief of joint pain, sprains, and sore muscles.

KEEP OUT OF REACH OF CHILDREN.

WARNINGS

Warnings: FOR EXTERNAL USE ONLY. Do not use if allergic to any ingredient. Consult a doctor before use for serious conditions, if conditions worsen or persist, or accidental ingestion occurs. If pregnant or nursing, consult a doctor before use. Avoid contact with eyes. Do not use if safety seal is broken or missing.

QUESTIONS

Questions? Call 866.642.2858 Made with care by Uriel, East Troy, WI 53120 www.urielpharmacy.com